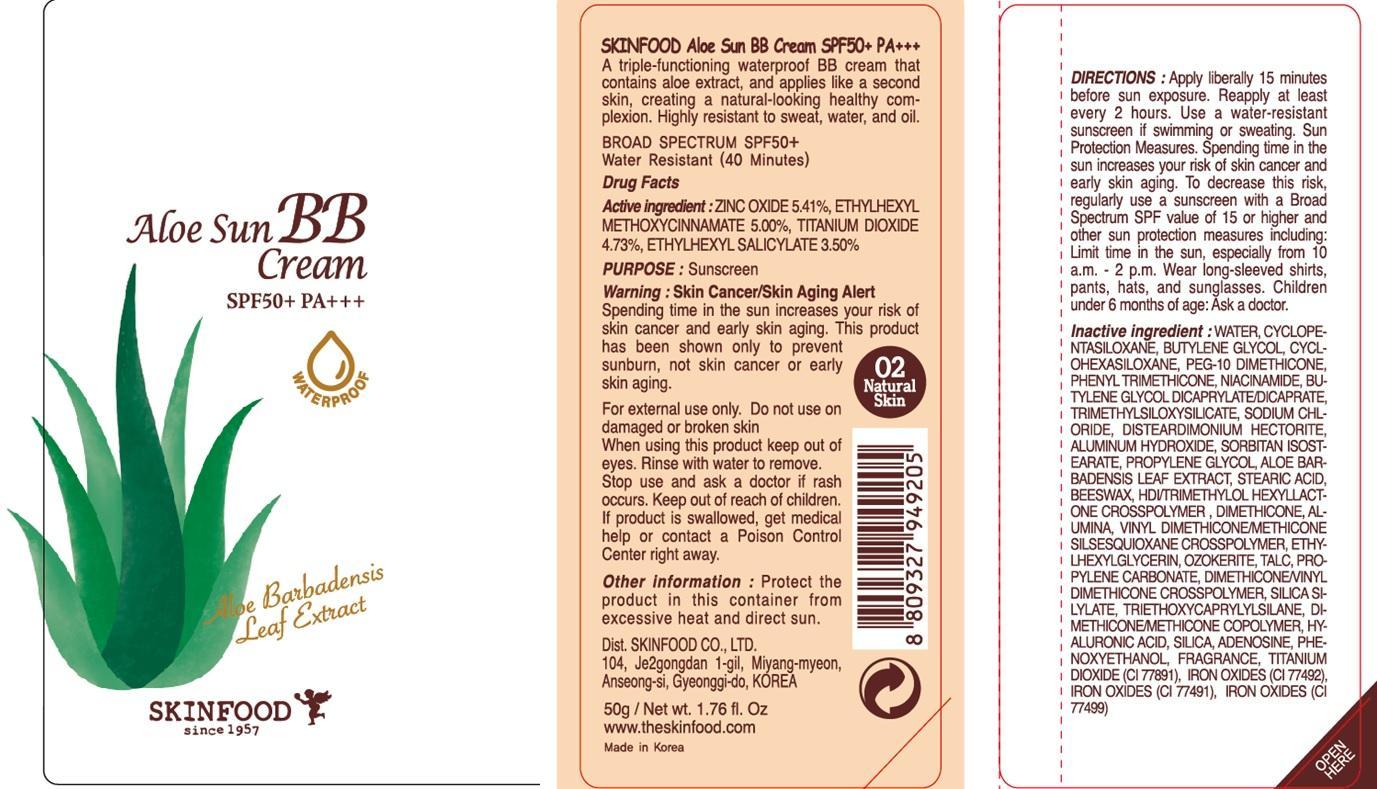 DRUG LABEL: ALOE SUN BB
NDC: 76214-046 | Form: CREAM
Manufacturer: SKINFOOD CO., LTD.
Category: otc | Type: HUMAN OTC DRUG LABEL
Date: 20140728

ACTIVE INGREDIENTS: ZINC OXIDE 2.70 g/50 g; OCTINOXATE 2.50 g/50 g; TITANIUM DIOXIDE 2.36 g/50 g; OCTISALATE 1.75 g/50 g
INACTIVE INGREDIENTS: WATER; BUTYLENE GLYCOL

ACTIVE INGREDIENT

Active ingredient: ZINC OXIDE 5.41%, ETHYLHEXYL METHOXYCINNAMATE 5.00%, TITANIUM DIOXIDE 4.73%, ETHYLHEXYL SALICYLATE 3.50%

INACTIVE INGREDIENT

WATER, CYCLOPENTASILOXANE, BUTYLENE GLYCOL, CYCLOHEXASILOXANE, PEG-10 DIMETHICONE, PHENYL TRIMETHICONE, NIACINAMIDE, BUTYLENE GLYCOL DICAPRYLATE/DICAPRATE, TRIMETHYLSILOXYSILICATE, SODIUM CHLORIDE, DISTEARDIMONIUM HECTORITE, ALUMINUM HYDROXIDE, SORBITAN ISOSTEARATE, PROPYLENE GLYCOL, ALOE BARBADENSIS LEAF EXTRACT, STEARIC ACID, BEESWAX, HDI/TRIMETHYLOL HEXYLLACTONE CROSSPOLYMER , DIMETHICONE, ALUMINA, VINYL DIMETHICONE/METHICONE SILSESQUIOXANE CROSSPOLYMER, ETHYLHEXYLGLYCERIN, OZOKERITE, TALC, PROPYLENE CARBONATE, DIMETHICONE/VINYL DIMETHICONE CROSSPOLYMER, SILICA SILYLATE, TRIETHOXYCAPRYLYLSILANE, DIMETHICONE/METHICONE COPOLYMER, HYALURONIC ACID, SILICA, ADENOSINE, PHENOXYETHANOL, FRAGRANCE, TITANIUM DIOXIDE (CI 77891), IRON OXIDES (CI 77492), IRON OXIDES (CI 77491), IRON OXIDES (CI 77499)

PURPOSE

PURPOSE: Sunscreen

WARNINGS

Warning: Skin Cancer/Skin Aging Alert
Spending time in the sun increases your risk of skin cancer and early skin aging. This product has been shown only to prevent sunburn, not skin cancer or early skin aging.

For external use only. Do not use on damaged or broken skin
When using this product keep out of eyes. Rinse with water to remove.
Stop use and ask a doctor if rash occurs. Keep out of reach of children.
If product is swallowed, get medical help or contact a Poison Control Center right away.

KEEP OUT OF REACH OF CHILDREN

USE

Helps prevent sunburn. If used as directed with other sun protection measures (see Directions), decreases the risk of skin cancer and early skin aging caused by the sun

DIRECTIONS

Apply liberally 15 minutes before sun exposure. Reapply at least every 2 hours. Use a water-resistant sunscreen if swimming or sweating. Sun Protection Measures. Spending time in the sun increases your risk of skin cancer and early skin aging. To decrease this risk, regularly use a sunscreen with a Broad Spectrum SPF value of 15 or higher and other sun protection measures including: Limit time in the sun, especially from 10 a.m. - 2 p.m. Wear long-sleeved shirts, pants, hats, and sunglasses. Children under 6 months of age: Ask a doctor.